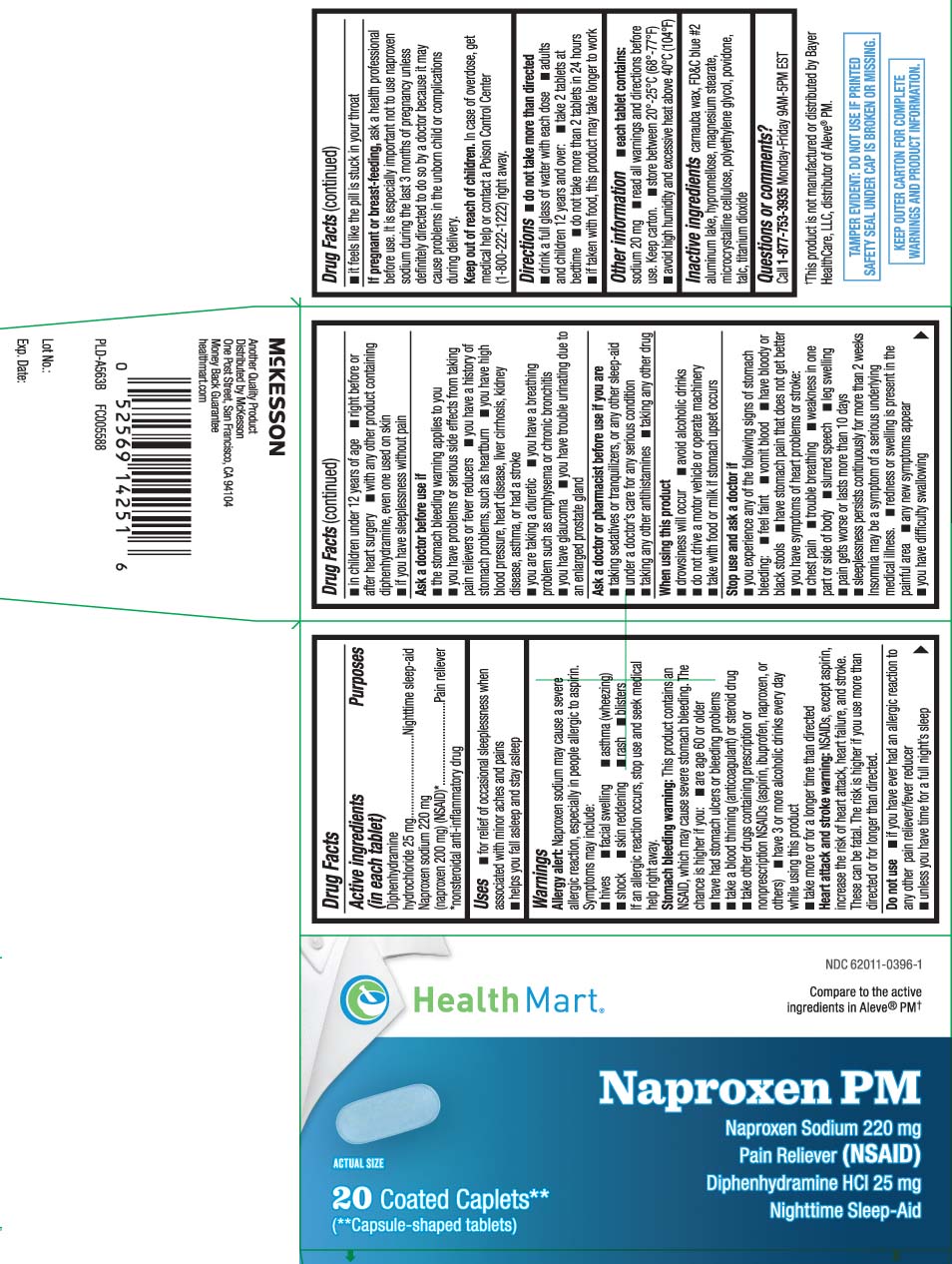 DRUG LABEL: Naproxen Sodium PM
NDC: 62011-0396 | Form: TABLET
Manufacturer: Strategic Sourcing Services LLC
Category: otc | Type: HUMAN OTC DRUG LABEL
Date: 20250820

ACTIVE INGREDIENTS: NAPROXEN SODIUM 220 mg/1 1; DIPHENHYDRAMINE HYDROCHLORIDE 25 mg/1 1
INACTIVE INGREDIENTS: CARNAUBA WAX; FD&C BLUE NO. 2; POLYETHYLENE GLYCOL, UNSPECIFIED; MAGNESIUM STEARATE; HYPROMELLOSES; POVIDONE; CELLULOSE, MICROCRYSTALLINE; TALC; TITANIUM DIOXIDE

Drug Facts

Active ingredient (in each caplet)

Diphenhydramine hydrochloride 25 mg

Naproxen sodium 220 mg (naproxen 200 mg) (NSAID)*

*nonsteroidal anti-inflammatory drug

Purpose

Nighttime sleep-aid

Pain reliever

Uses

- for relief of occasional sleeplessness when associated with minor aches and pains
- help you fall asleep and stay asleep

Warnings

Allergy alert: Naproxen sodium may cause a severe allergic reaction, especially in people allergic to aspirin. Symptoms may include:

- hives
- facial swelling
- asthma (wheezing)
- shock
- skin reddening
- rash
- blisters

If an allergic reaction occurs, stop use and seek medical help right away.

Stomach bleeding warning: This product contains an NSAID, which may cause severe stomach bleeding. The chance is higher if you:

- are age 60 or older
- have had stomach ulcers or bleeding problems
- take a blood thinning (anticoagulant) or steroid drug
- have 3 or more alcoholic drinks every day while using this product
- take other drugs containing prescription or nonprescription NSAIDs (aspirin, ibuprofen, naproxen, or others)
- take more or for a longer time than directed

Heart attack and stroke warning: NSAIDs, except aspirin, increase the risk of heart attack, heart failure, and stroke. These can be fatal. The risk is higher if you use more than directed or for longer than directed

Do not use

- if you have ever had an allergic reaction to any other pain reliever/fever reducer
- unless you have time for a full night's sleep
- in children under 12 years of age
- right before or after heart surgery
- with any other product containing diphenhydramine, even one used on skin
- if you have sleeplessness without pain

Ask a doctor before use if

- the stomach bleeding warning applies to you
- you have problems or serious side effects from taking pain relievers or fever reducer
- you have a history of stomach problems, such as heartburn
- you have high blood pressure, heart disease, liver cirrhosis, kidney disease, asthma, or had a stroke
- you are taking a diuretic
- you have a breathing such as emphysema or chronic bronchitis
- you have glaucoma
- you have trouble urinating due to an enlarged prostate gland

Ask a doctor or pharmacist before use if you are

- taking sedatives or tranquilizer, or any other sleep-aid
- under a doctor’s care for any serious condition
- taking any other antihistamines
- taking any other drug

When using this product

- drowsiness will occur
- avoid alcoholic drinks
- do not drive a motor vehicle or operate machinery
- take with food or milk if stomach upset occurs

Stop use and ask a doctor if

- you experience any of the following signs of stomach bleeding:
  - feel faint
  - have bloody or black stools
  - vomit blood
  - have stomach pain that does not get better
- you have symptoms of heart problems or stroke
  - chest pain
  - trouble breathing
  - weakness in one part or side of body
  - slurred speech
  - leg swelling
- pain gets worse or last more than 10 days
- sleeplessness persists continuously for more than 2 weeks insomnia may be a symptom of a serious underlying medical illness.
- redness or swelling is present in the painful area
- any new symptoms appear
- you have difficulty swallowing
- it feels like the pill is stuck in your throat

If pregnant or breast-feeding,

ask a health professional before use. It is especially important not to use naproxen sodium during the last 3 months of pregnancy unless definitely directed to do so by a doctor because it may cause problems in the unborn child or complications during delivery.

Keep out of reach of children.

In case of overdose, get medical help or contact a Poison Control Center (1-800-222-1222) right away.

Directions

- do not take more than directed
- drink a full glass of water with each dose
- adults and children 12 years and over:
- take 2 tablets at bedtime
- do not take more than 2 tablets in 24 hours
- if taken with food, this product may take longer to work

Other information

- each tablet contains: sodium 20 mg
- read all warnings and directions before use. Keep carton.
- store between 20º- 25ºC (68º-77ºF)
- avoid high humidity and excessive heat above 40ºC (104ºF)

Inactive ingredients

carnauba wax, FD&C blue #2, aluminum lake, hypromellose, magnesium stearate, microcrystalline cellulose, polyethylene glycol, povidone, talc, titanium dioxide

Questions or comments?

Call 1-877-753-3935 Monday-Friday 9AM-5PM EST

Principal Display Panel

Compare to the active ingredients in Aleve® PM†

Naproxen PM

Naproxen Sodium 220 mg

Pain reliever (NSAID)

Diphenhydramine HCI 25 mg/

Nighttime sleep-aid

COATED CAPLETS**

(**Capsule-shaped tablets)

†This product is not manufactured or distributed by Bayer Health Care, LLC, distributor of Aleve® PM

TAMPER EVIDENT: DO NOT USE IF PRINTED SAFETY SEAL UNDER CAP IS BROKEN OR MISSING.

KEEP OUTER CARTON FOR COMPLETE WARNINGS AND PRODUCT INGORMATION.

Another Quality Product

Distributed by McKesson

One Post Street, San Francisco, CA 94104

healthmart.com

Product Label

HEALTH MART Naproxen PM